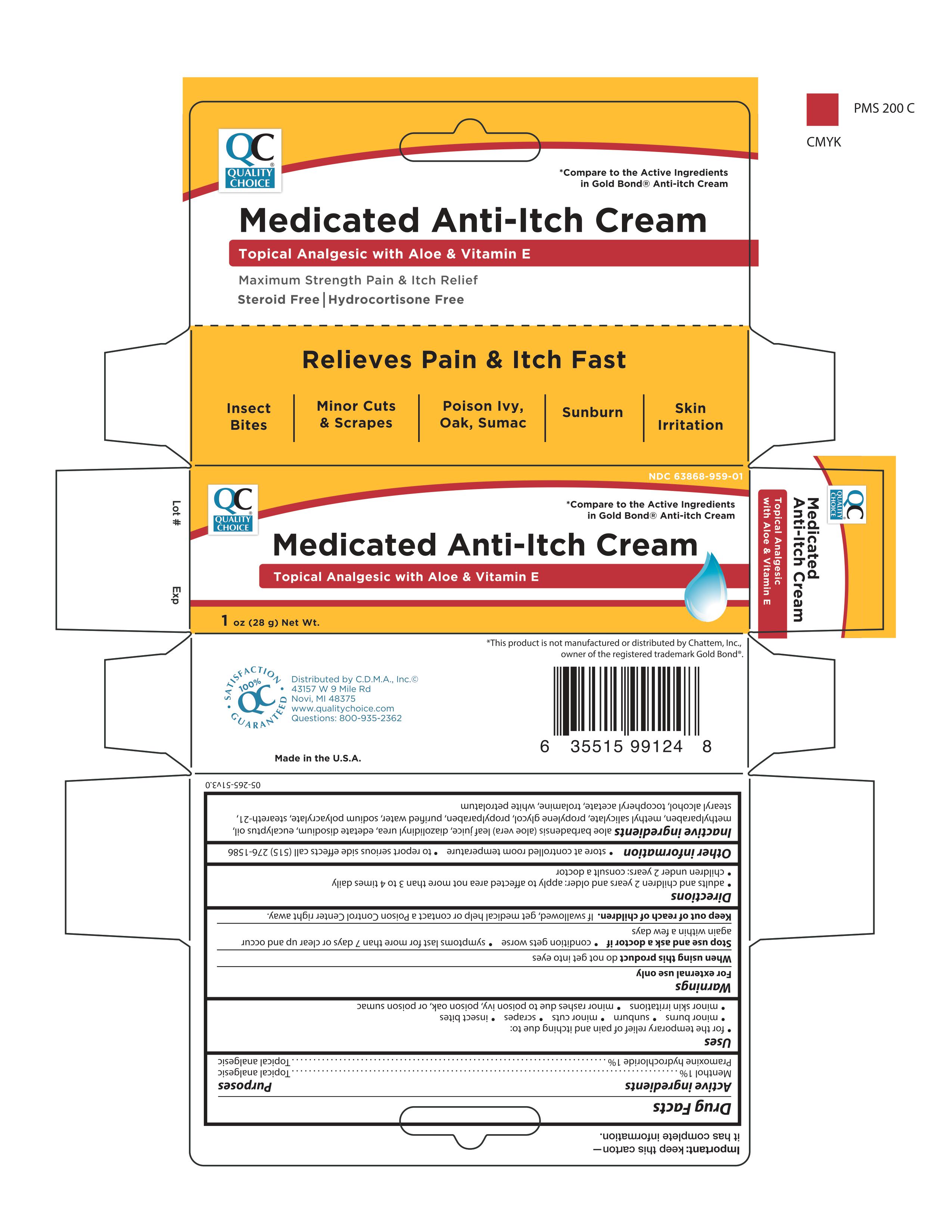 DRUG LABEL: QC Medicated anti itch
NDC: 63868-959 | Form: CREAM
Manufacturer: Chain Drug Marketing Association
Category: otc | Type: HUMAN OTC DRUG LABEL
Date: 20241208

ACTIVE INGREDIENTS: MENTHOL 1 g/100 g; PRAMOXINE HYDROCHLORIDE 1 g/100 g
INACTIVE INGREDIENTS: WATER; DIAZOLIDINYL UREA; TROLAMINE; STEARETH-21; PETROLATUM; METHYLPARABEN; PROPYLPARABEN; SODIUM POLYACRYLATE (8000 MW); PROPYLENE GLYCOL; METHYL SALICYLATE; EDETATE DISODIUM; ALOE VERA LEAF; STEARYL ALCOHOL; EUCALYPTUS OIL; .ALPHA.-TOCOPHEROL ACETATE, DL-

QC Medicated Anti Itch Cream

Active Ingredient

Menthol 1%

Pramoxine hydrochloride 1%

Uses

for the temporary relief of pain and itching due to: minor burns, sunburn, minor cuts, scrapes, insect bites, minor skin irritations ,minor rashes due to poison ivy, poison oak, or poison sumac

Purpose

Topical anagesic

Warnings

For external use only

When using this product

do not get into eyes

Keep out of reach of children

If swallowed, get medical help or contact a Poison Control Center right away.

Other Information

store at controlled room temperature

Directions

adults and children 2 years and older: apply to affected area not more than 3 to 4 times daily

children under 2 years: consult a doctor

Dosage

Adults and Children 2 years and older: Apply to affected are not more than 3 to 4 times daily.

Inactive Ingredients

aloe barbadensis (aloe vera) leaf juice, diazolidinyl urea, edetate disodium, eucalyptus oil, methylparaben, methyl salicylate, mineral oil, PPG-1 trideceth-6, propylene glycol, propylparaben, purified water, sodium acrylates copolymer, steareth-21, stearyl alcohol, tocopheryl acetate, trolamine, white petrolatum